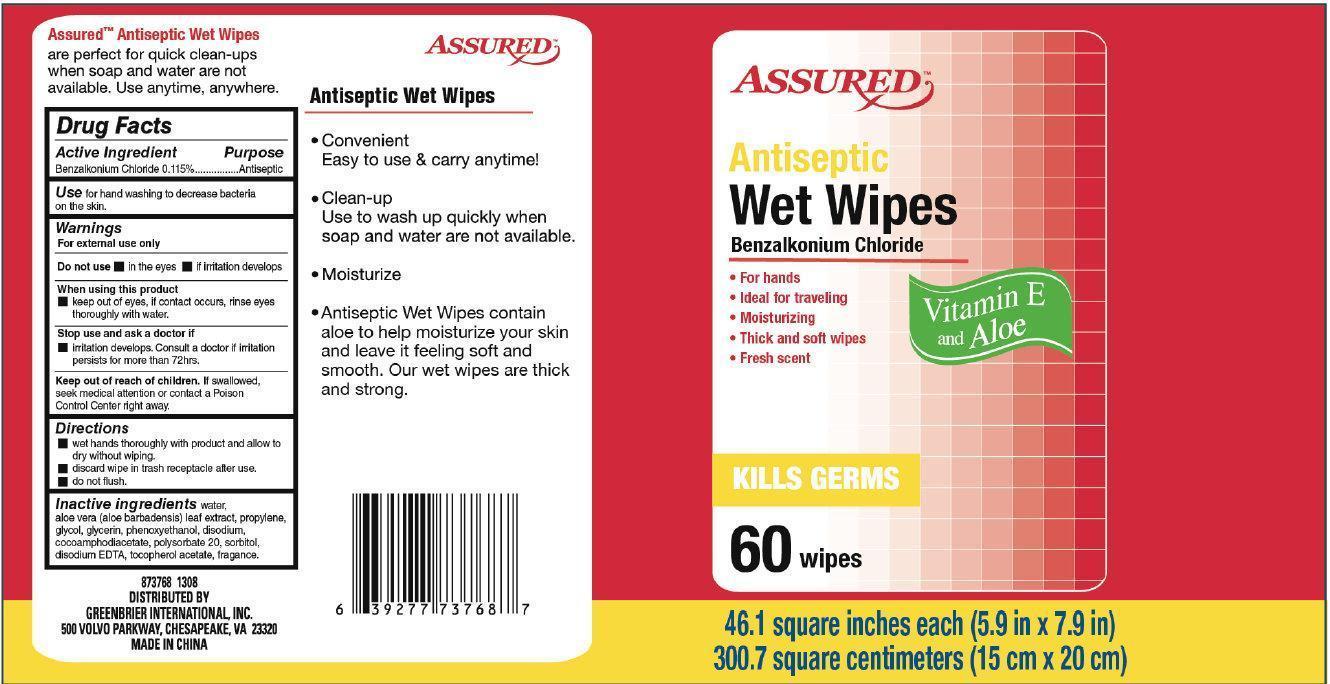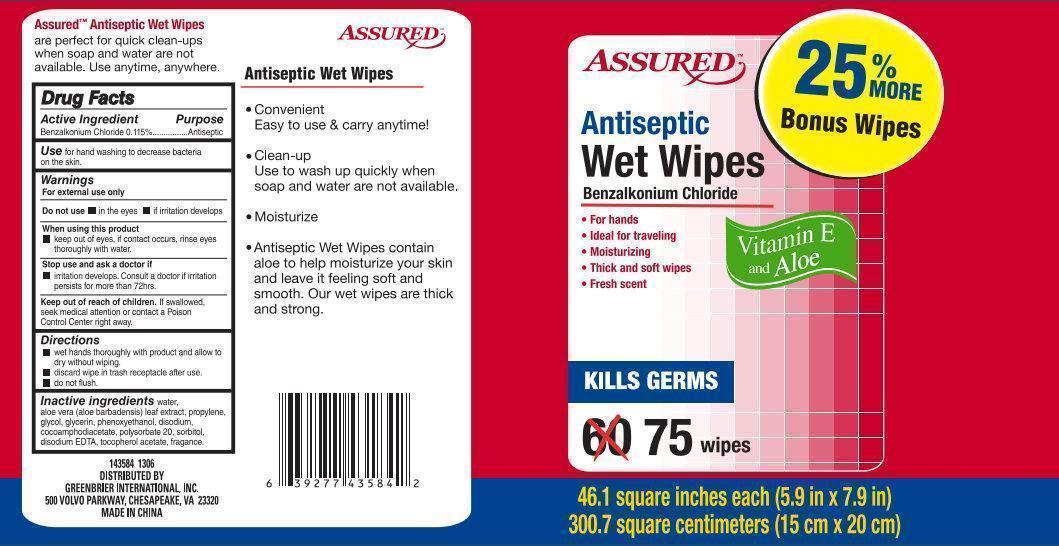 DRUG LABEL: ASSURED Antiseptic Wet Wipes Vitamin E and Aloe
NDC: 33992-5111 | Form: LIQUID
Manufacturer: Greenbrier International, Inc.
Category: otc | Type: HUMAN OTC DRUG LABEL
Date: 20190417

ACTIVE INGREDIENTS: BENZALKONIUM CHLORIDE 0.115 g/100 g
INACTIVE INGREDIENTS: WATER; ALOE; PROPYLENE GLYCOL; GLYCERIN; PHENOXYETHANOL; DISODIUM COCOAMPHODIACETATE; POLYSORBATE 20; SORBITOL; EDETATE DISODIUM; .ALPHA.-TOCOPHEROL ACETATE

ASSURED Antiseptic Wet Wipes Vitamin E and Aloe

Active Ingredient

Benzalkonium chloride 0.115%

Purpose

Antiseptic

Uses

For hand washing to decrease bacteria on the skin.

Warnings

For external use only

Do not use

- in the eyes
- if irritation develops

When using this product

- Keep out of eyes, if contact occures, rinse eyes thoroughly with water.

Stop use and ask a doctor if

- irritation develops. Consult a doctor if irritation persists for more than 72hrs.

Keep out of the reach of children

If swallowed, seek medical attention or contact Poison Control Center right away.

Directions

- Wet hands thoroughly with product and allow to dry without wiping.
- discard wipe in trash receptacle after use.
- do not flush.

Inactive ingredients

water, aloe vera (aloe barbadensis) leaf extract, propylene, glycol, glycerin, phenoxyethanol, disodium, cocoamphodiacetate, polysorbate 20, sorbitol, disodium EDTA, tocopherol acetate, fragance.